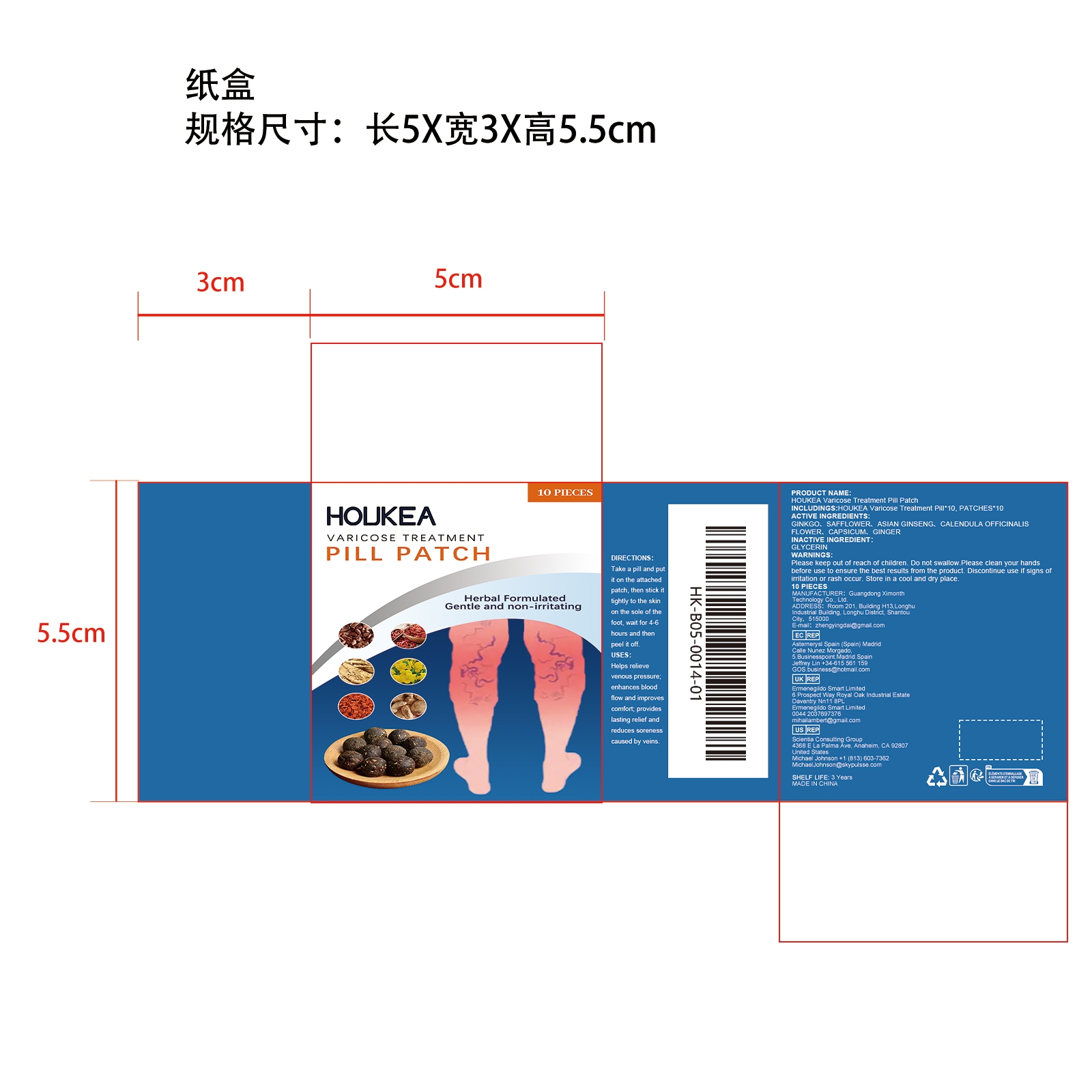 DRUG LABEL: HOUKEA Varicose Treatment Pill Patch
NDC: 84660-101 | Form: PATCH
Manufacturer: Guangdong Ximonth Technology Co., Ltd.
Category: otc | Type: HUMAN OTC DRUG LABEL
Date: 20241031

ACTIVE INGREDIENTS: CAPSICUM 1 mg/10 mg; GINGER 1 mg/10 mg; CALENDULA OFFICINALIS FLOWER 1 mg/10 mg; ASIAN GINSENG 1 mg/10 mg; SAFFLOWER 1 mg/10 mg; GINKGO 1 mg/10 mg
INACTIVE INGREDIENTS: GLYCERIN 4 mg/10 mg

Active Ingredient(s)

GINKGO、SAFFLOWER、ASIAN GINSENG、CALENDULA OFFICINALIS FLOWER、CAPSICUM、GINGER

Purpose

Helps relievevenous pressure; enhances blood flow and improves comfort; provides lasting relief and reduces soreness caused by veins.

Use

Take a pill and put it on the attached patch, then stick it tightly to the skin on the sole of the foot, wait for 4-6 hours and then peel it off.

Warnings

Please keep out of reach of children.Do not swallow.Please clean your hands before use to ensure the best results from the product.Discontinue use if signs of irritation or rash occur.Store in a cool and dry place.

Do not use

Discontinue use if signs of irritation or rash occur.

Stop Use

Discontinue use if signs of irritation or rash occur.

KEEP OUT OF REACH OF CHILDREN

Please keep out of reach of children. Do not swallow.

SAFE HANDLING WARNING

Store in a cool and dry place.

INACTIVE INGREDIENT

GLYCERIN